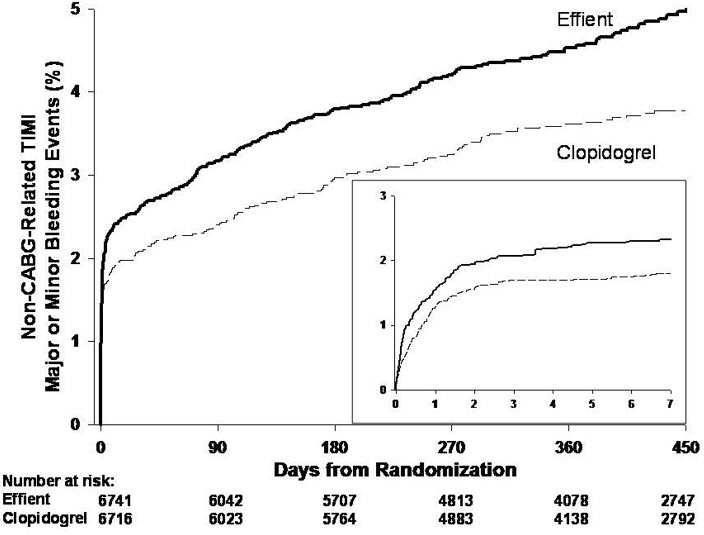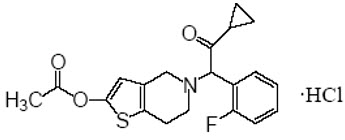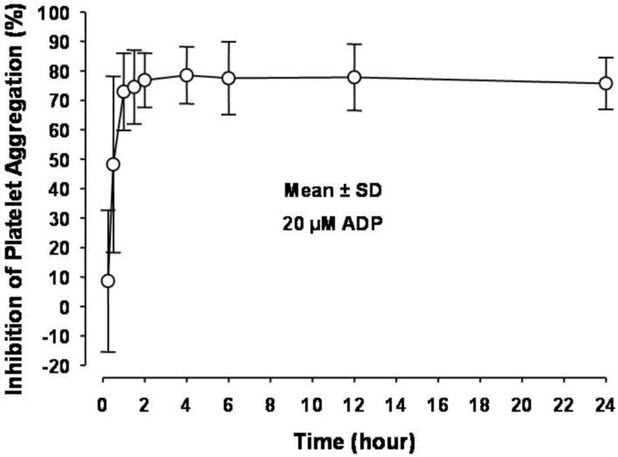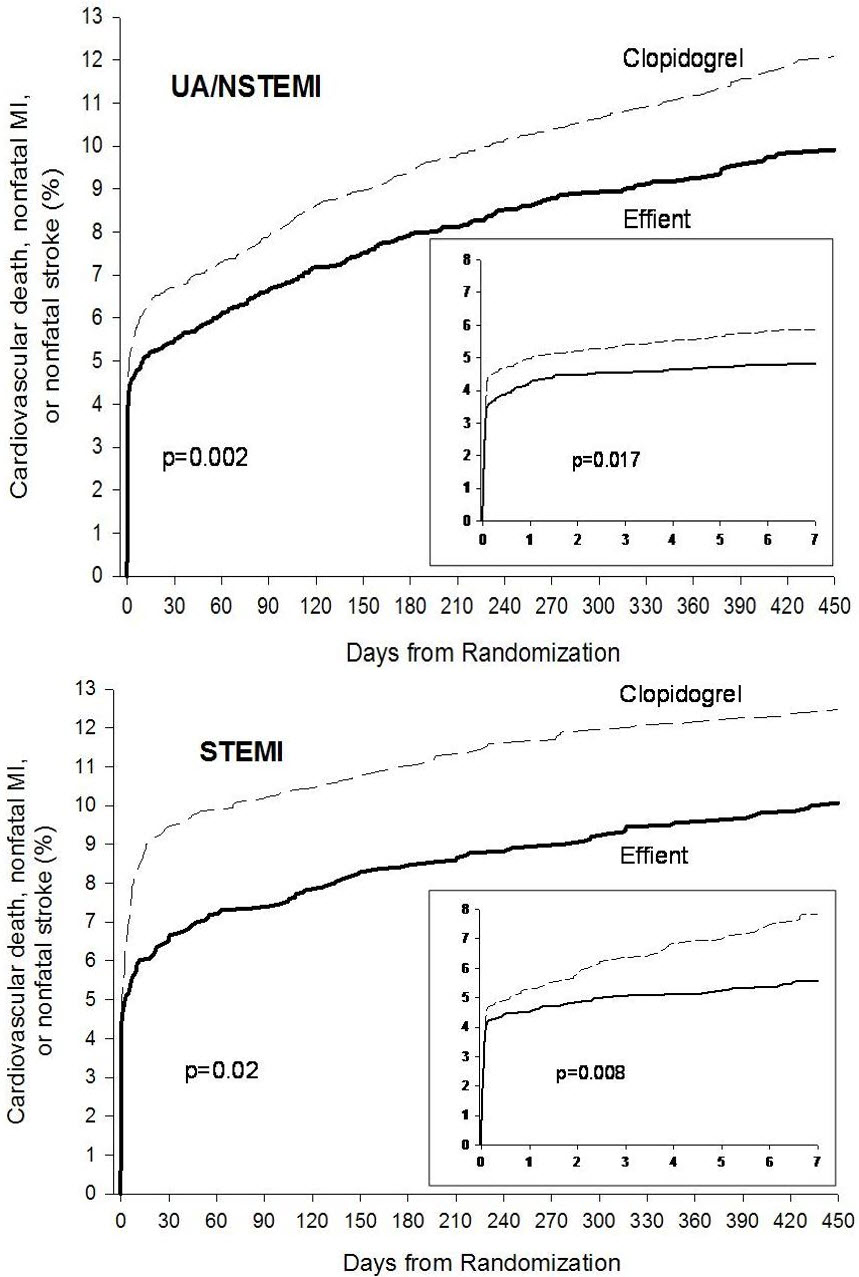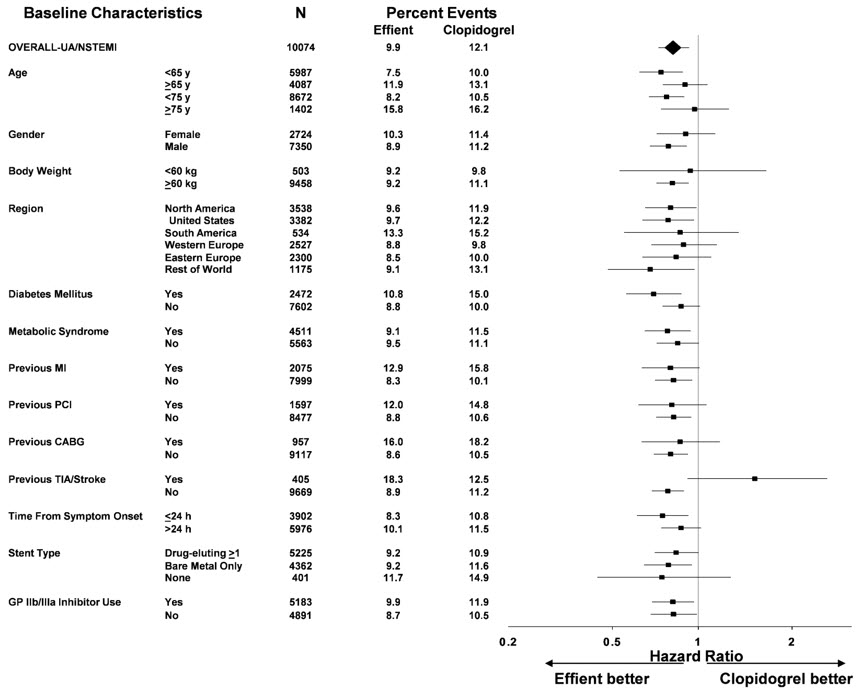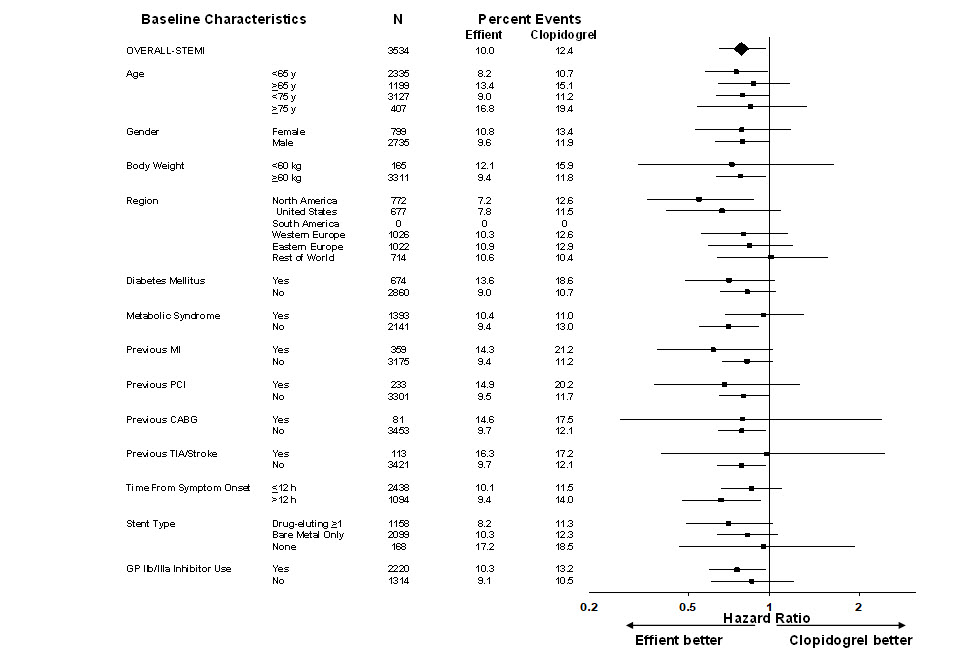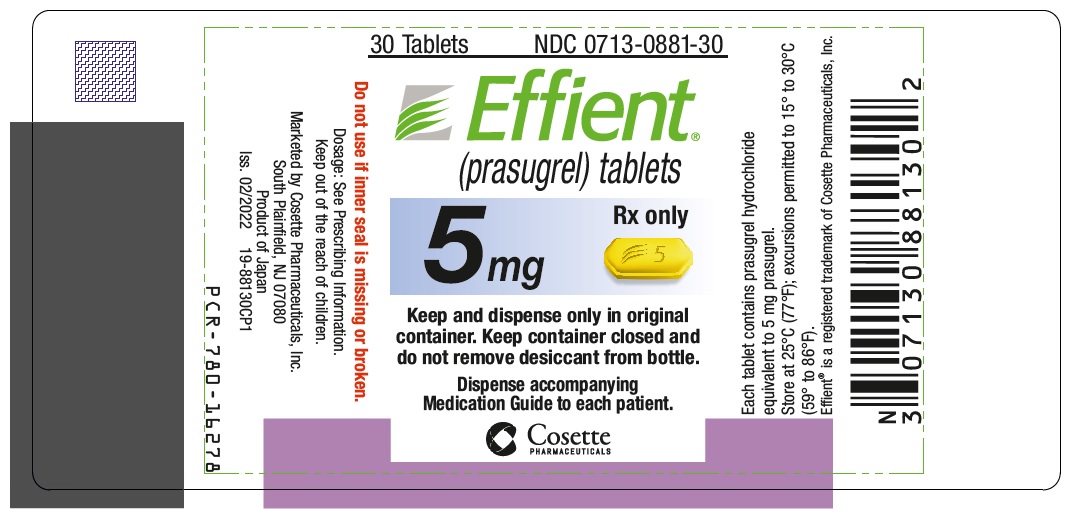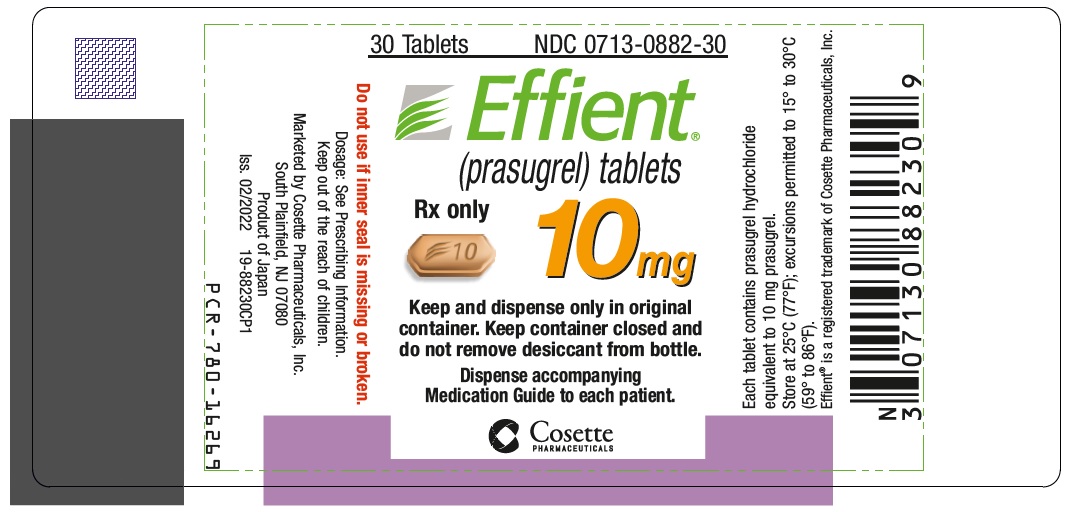 DRUG LABEL: Effient
NDC: 0713-0881 | Form: TABLET, COATED
Manufacturer: Cosette Pharmaceuticals, Inc.
Category: prescription | Type: HUMAN PRESCRIPTION DRUG LABEL
Date: 20220907

ACTIVE INGREDIENTS: PRASUGREL HYDROCHLORIDE 5 mg/1 1
INACTIVE INGREDIENTS: MANNITOL; HYPROMELLOSE, UNSPECIFIED; LOW-SUBSTITUTED HYDROXYPROPYL CELLULOSE, UNSPECIFIED; MICROCRYSTALLINE CELLULOSE; SUCROSE STEARATE; GLYCERYL DIBEHENATE; LACTOSE MONOHYDRATE; HYPROMELLOSE 2910 (15 MPA.S); TITANIUM DIOXIDE; TRIACETIN; FERRIC OXIDE YELLOW

HIGHLIGHTS OF PRESCRIBING INFORMATION

These highlights do not include all the information needed to use EFFIENT safely and effectively. See full prescribing information for EFFIENT.
EFFIENT® (prasugrel) tablets, for oral use
Initial U.S. Approval: 2009

WARNING: BLEEDING RISK

See full prescribing information for complete boxed warning.

- Effient can cause significant, sometimes fatal, bleeding (5.1, 5.2, 6.1).
- Do not use Effient in patients with active pathological bleeding or a history of transient ischemic attack or stroke (4.1, 4.2).
- In patients ≥75 years of age, Effient is generally not recommended, except in high-risk patients (diabetes or prior myocardial infarction [MI]), where its use may be considered (8.5).
- Do not start Effient in patients likely to undergo urgent coronary artery bypass graft surgery (CABG). When possible, discontinue Effient at least 7 days prior to any surgery (5.2).
- Additional risk factors for bleeding include: body weight <60 kg, propensity to bleed, concomitant use of medications that increase the risk of bleeding (5.1).
- Suspect bleeding in any patient who is hypotensive and has recently undergone invasive or surgical procedures (5.1).
- If possible, manage bleeding without discontinuing Effient. Stopping Effient increases the risk of subsequent cardiovascular events (5.3).

1 INDICATIONS AND USAGE

Effient is a P2Y12 platelet inhibitor indicated for the reduction of thrombotic cardiovascular events (including stent thrombosis) in patients with acute coronary syndrome who are to be managed with percutaneous coronary intervention (PCI) as follows:

- Patients with unstable angina or non-ST-elevation myocardial infarction (NSTEMI) (1.1).
- Patients with ST-elevation myocardial infarction (STEMI) when managed with either primary or delayed PCI (1.1).

2 DOSAGE AND ADMINISTRATION

- Initiate treatment with a single 60 mg oral loading dose (2).
- Continue at 10 mg once daily with or without food. Consider 5 mg once daily for patients <60 kg (2).
- Patients should also take aspirin (75 mg to 325 mg) daily (2).

3 DOSAGE FORMS AND STRENGTHS

5 mg and 10 mg tablets (3)

4 CONTRAINDICATIONS

- Active pathological bleeding (4.1)
- Prior transient ischemic attack or stroke (4.2)
- Hypersensitivity to prasugrel or any component of the product (4.3)

5 WARNINGS AND PRECAUTIONS

- CABG-related bleeding: Risk increases in patients receiving Effient who undergo CABG (5.2).
- Discontinuation of Effient: Premature discontinuation increases risk of stent thrombosis, MI, and death (5.3).
- Thrombotic thrombocytopenic purpura (TTP): TTP has been reported with Effient (5.4).
- Hypersensitivity: Hypersensitivity including angioedema has been reported with Effient including in patients with a history of hypersensitivity reaction to other thienopyridines (5.5).

6 ADVERSE REACTIONS

Bleeding, including life-threatening and fatal bleeding, is the most commonly reported adverse reaction (6.1).

To report SUSPECTED ADVERSE REACTIONS, contact Cosette Pharmaceuticals, Inc. at 1-800-922-1038 or FDA at 1-800-FDA-1088 or www.fda.gov/medwatch.

7 DRUG INTERACTIONS

Opioids: Decreased exposure to prasugrel. Consider use of parenteral antiplatelet agent (7.3).

FULL PRESCRIBING INFORMATION

WARNING: BLEEDING RISK

- Effient can cause significant, sometimes fatal, bleeding [see Warnings and Precautions (5.1, 5.2) and Adverse Reactions (6.1)] .
- Do not use Effient in patients with active pathological bleeding or a history of transient ischemic attack (TIA) or stroke [see Contraindications (4.1, 4.2)] .
- In patients ≥75 years of age, Effient is generally not recommended, because of the increased risk of fatal and intracranial bleeding and uncertain benefit, except in high-risk situations (patients with diabetes or a history of prior myocardial infarction [MI]) where its effect appears to be greater and its use may be considered [see Use in Specific Populations (8.5)] .
- Do not start Effient in patients likely to undergo urgent coronary artery bypass graft surgery (CABG). When possible, discontinue Effient at least 7 days prior to any surgery [see Warnings and Precautions (5.2)] .
- Additional risk factors for bleeding include: body weight <60 kg, propensity to bleed, concomitant use of medications that increase the risk of bleeding (e.g ., warfarin, heparin, fibrinolytic therapy, chronic use of nonsteroidal anti-inflammatory drugs [NSAIDs]) [see Warnings and Precautions (5.1)] .
- Suspect bleeding in any patient who is hypotensive and has recently undergone coronary angiography, percutaneous coronary intervention (PCI), CABG, or other surgical procedures in the setting of Effient [see Warnings and Precautions (5.1)] .
- If possible, manage bleeding without discontinuing Effient. Discontinuing Effient, particularly in the first few weeks after acute coronary syndrome, increases the risk of subsequent cardiovascular (CV) events [see Warnings and Precautions (5.3)] .

1 INDICATIONS AND USAGE

1.1 Acute Coronary Syndrome

Effient® is indicated to reduce the rate of thrombotic CV events (including stent thrombosis) in patients with acute coronary syndrome (ACS) who are to be managed with percutaneous coronary intervention (PCI) as follows:

- Patients with unstable angina (UA) or non-ST-elevation myocardial infarction (NSTEMI).
- Patients with ST-elevation myocardial infarction (STEMI) when managed with primary or delayed PCI.

Effient has been shown to reduce the rate of a combined endpoint of cardiovascular death, nonfatal myocardial infarction (MI), or nonfatal stroke compared to clopidogrel. The difference between treatments was driven predominantly by MI, with no difference on strokes and little difference on CV death [see Clinical Studies (14)] .

2 DOSAGE AND ADMINISTRATION

Initiate Effient treatment as a single 60 mg oral loading dose and then continue at 10 mg orally once daily. Patients taking Effient should also take aspirin (75 mg to 325 mg) daily [see Drug Interactions (7.4) and Clinical Pharmacology (12.3)] . Effient may be administered with or without food [see Clinical Pharmacology (12.3) and Clinical Studies (14)] .

Timing of Loading Dose

In the clinical trial that established the efficacy and safety of Effient, the loading dose of Effient was not administered until coronary anatomy was established in UA/NSTEMI patients and in STEMI patients presenting more than 12 hours after symptom onset. In STEMI patients presenting within 12 hours of symptom onset, the loading dose of Effient was administered at the time of diagnosis, although most received Effient at the time of PCI [see Clinical Studies (14)] . For the small fraction of patients that required urgent CABG after treatment with Effient, the risk of significant bleeding was substantial.

Although it is generally recommended that antiplatelet therapy be administered promptly in the management of ACS because many cardiovascular events occur within hours of initial presentation, in a trial of 4033 NSTEMI patients, no clear benefit was observed when Effient loading dose was administered prior to diagnostic coronary angiography compared to at the time of PCI; however, risk of bleeding was increased with early administration in patients undergoing PCI or early CABG.

Dosing in Low Weight Patients

Compared to patients weighing ≥60 kg, patients weighing <60 kg have an increased exposure to the active metabolite of prasugrel and an increased risk of bleeding on a 10 mg once daily maintenance dose. Consider lowering the maintenance dose to 5 mg in patients <60 kg. The effectiveness and safety of the 5 mg dose have not been prospectively studied [see Warnings and Precautions (5.1), Adverse Reactions (6.1), and Clinical Pharmacology (12.3)] .

3 DOSAGE FORMS AND STRENGTHS

Effient 5 mg is available as a yellow, elongated hexagonal, film-coated, non-scored tablet debossed with "5121" on one side and 3 parallel arched lines followed by a "5" on the other side.

Effient 10 mg is available as a beige, elongated hexagonal, film-coated, non-scored tablet debossed with "5123" on one side and 3 parallel arched lines followed by a "10" on the other side.

4 CONTRAINDICATIONS

4.1 Active Bleeding

Effient is contraindicated in patients with active pathological bleeding such as peptic ulcer or intracranial hemorrhage (ICH) [see Warnings and Precautions (5.1) and Adverse Reactions (6.1)] .

4.2 Prior Transient Ischemic Attack or Stroke

Effient is contraindicated in patients with a history of prior transient ischemic attack (TIA) or stroke. In TRITON-TIMI 38 (TRial to Assess Improvement in Therapeutic Outcomes by Optimizing Platelet Inhibitio N with Prasugrel), patients with a history of TIA or ischemic stroke (>3 months prior to enrollment) had a higher rate of stroke on Effient (6.5%; of which 4.2% were thrombotic stroke and 2.3% were intracranial hemorrhage [ICH]) than on clopidogrel (1.2%; all thrombotic). In patients without such a history, the incidence of stroke was 0.9% (0.2% ICH) and 1.0% (0.3% ICH) with Effient and clopidogrel, respectively. Patients with a history of ischemic stroke within 3 months of screening and patients with a history of hemorrhagic stroke at any time were excluded from TRITON-TIMI 38. Patients who experience a stroke or TIA while on Effient generally should have therapy discontinued [see Adverse Reactions (6.1) and Clinical Studies (14)] .

4.3 Hypersensitivity

Effient is contraindicated in patients with hypersensitivity (e.g., anaphylaxis) to prasugrel or any component of the product [see Adverse Reactions (6.2)] .

5 WARNINGS AND PRECAUTIONS

5.1 General Risk of Bleeding

Thienopyridines, including Effient, increase the risk of bleeding. With the dosing regimens used in TRITON-TIMI 38, TIMI (Thrombolysis in Myocardial Infarction) Major (clinically overt bleeding associated with a fall in hemoglobin ≥5 g/dL, or intracranial hemorrhage) and TIMI Minor (overt bleeding associated with a fall in hemoglobin of ≥3 g/dL but <5 g/dL), bleeding events were more common on Effient than on clopidogrel [see Adverse Reactions (6.1)] . The bleeding risk is highest initially, as shown in Figure 1 (events through 450 days; inset shows events through 7 days).

Figure 1: Non-CABG-Related TIMI Major or Minor Bleeding Events

Suspect bleeding in any patient who is hypotensive and has recently undergone coronary angiography, PCI, CABG, or other surgical procedures even if the patient does not have overt signs of bleeding.

Do not use Effient in patients with active bleeding, prior TIA or stroke [see Contraindications (4.1, 4.2)] .

Other risk factors for bleeding are:

- Age ≥75 years. Because of the risk of bleeding (including fatal bleeding) and uncertain effectiveness in patients ≥75 years of age, use of Effient is generally not recommended in these patients, except in high-risk situations (patients with diabetes or history of myocardial infarction) where its effect appears to be greater and its use may be considered [see Adverse Reactions (6.1), Use in Specific Populations (8.5), Clinical Pharmacology (12.3), and Clinical Studies (14)] .
- CABG or other surgical procedure [see Warnings and Precautions (5.2)] .
- Body weight <60 kg. Consider a lower (5 mg) maintenance dose [see Dosage and Administration (2), Adverse Reactions (6.1), and Use in Specific Populations (8.6)] .
- Propensity to bleed (e.g., recent trauma, recent surgery, recent or recurrent gastrointestinal (GI) bleeding, active peptic ulcer disease, severe hepatic impairment, or moderate to severe renal impairment) [see Adverse Reactions (6.1) and Use in Specific Populations (8.7, 8.8)] .
- Medications that increase the risk of bleeding (e.g., oral anticoagulants, chronic use of nonsteroidal anti-inflammatory drugs [NSAIDs], and fibrinolytic agents). Aspirin and heparin were commonly used in TRITON-TIMI 38 [see Drug Interactions (7.1, 7.2, 7.4) and Clinical Studies (14)] .

Thienopyridines inhibit platelet aggregation for the lifetime of the platelet (7-10 days), so withholding a dose will not be useful in managing a bleeding event or the risk of bleeding associated with an invasive procedure. Because the half-life of prasugrel's active metabolite is short relative to the lifetime of the platelet, it may be possible to restore hemostasis by administering exogenous platelets; however, platelet transfusions within 6 hours of the loading dose or 4 hours of the maintenance dose may be less effective.

5.2 Coronary Artery Bypass Graft Surgery-Related Bleeding

The risk of bleeding is increased in patients receiving Effient who undergo CABG. If possible, Effient should be discontinued at least 7 days prior to CABG.

Of the 437 patients who underwent CABG during TRITON-TIMI 38, the rates of CABG-related TIMI Major or Minor bleeding were 14.1% in the Effient group and 4.5% in the clopidogrel group [see Adverse Reactions (6.1)] . The higher risk for bleeding events in patients treated with Effient persisted up to 7 days from the most recent dose of study drug. For patients receiving a thienopyridine within 3 days prior to CABG, the frequencies of TIMI Major or Minor bleeding were 26.7% (12 of 45 patients) in the Effient group, compared with 5.0% (3 of 60 patients) in the clopidogrel group. For patients who received their last dose of thienopyridine within 4 to 7 days prior to CABG, the frequencies decreased to 11.3% (9 of 80 patients) in the prasugrel group and 3.4% (3 of 89 patients) in the clopidogrel group.

Do not start Effient in patients likely to undergo urgent CABG. CABG-related bleeding may be treated with transfusion of blood products, including packed red blood cells and platelets; however, platelet transfusions within 6 hours of the loading dose or 4 hours of the maintenance dose may be less effective.

5.3 Discontinuation of Effient

Discontinue thienopyridines, including Effient, for active bleeding, elective surgery, stroke, or TIA. The optimal duration of thienopyridine therapy is unknown. In patients who are managed with PCI and stent placement, premature discontinuation of any antiplatelet medication, including thienopyridines, conveys an increased risk of stent thrombosis, myocardial infarction, and death. Patients who require premature discontinuation of a thienopyridine will be at increased risk for cardiac events. Lapses in therapy should be avoided, and if thienopyridines must be temporarily discontinued because of an adverse event(s), they should be restarted as soon as possible [see Contraindications (4.1, 4.2) and Warnings and Precautions (5.1)] .

5.4 Thrombotic Thrombocytopenic Purpura (TTP)

TTP has been reported with the use of Effient. TTP can occur after a brief exposure (<2 weeks). TTP is a serious condition that can be fatal and requires urgent treatment, including plasmapheresis (plasma exchange). TTP is characterized by thrombocytopenia, microangiopathic hemolytic anemia (schistocytes [fragment red blood cells] seen on peripheral smear), neurological findings, renal dysfunction, and fever [see Adverse Reactions (6.2)] .

5.5 Hypersensitivity Including Angioedema

Hypersensitivity including angioedema has been reported in patients receiving Effient, including patients with a history of hypersensitivity reaction to other thienopyridines [see Contraindications (4.3) and Adverse Reactions (6.2)] .

6 ADVERSE REACTIONS

The following serious adverse reactions are also discussed elsewhere in the labeling:

- Bleeding [see Boxed Warning and Warnings and Precautions (5.1, 5.2)]
- Thrombotic Thrombocytopenic Purpura [see Warnings and Precautions (5.4)]
- Hypersensitivity Including Angioedema [see Warnings and Precautions (5.5)]

6.1 Clinical Trials Experience

Safety in patients with ACS undergoing PCI was evaluated in a clopidogrel-controlled study, TRITON-TIMI 38, in which 6741 patients were treated with Effient (60 mg loading dose and 10 mg once daily) for a median of 14.5 months (5802 patients were treated for over 6 months; 4136 patients were treated for more than 1 year). The population treated with Effient was 27 to 96 years of age, 25% female, and 92% Caucasian. All patients in the TRITON-TIMI 38 study were to receive aspirin. The dose of clopidogrel in this study was a 300 mg loading dose and 75 mg once daily.

Because clinical trials are conducted under widely varying conditions, adverse reaction rates observed in the clinical trials of a drug cannot be directly compared with the rates observed in other clinical trials of another drug and may not reflect the rates observed in practice.

Drug Discontinuation

The rate of study drug discontinuation because of adverse reactions was 7.2% for Effient and 6.3% for clopidogrel. Bleeding was the most common adverse reaction leading to study drug discontinuation for both drugs (2.5% for Effient and 1.4% for clopidogrel).

Bleeding

Bleeding Unrelated to CABG Surgery

In TRITON-TIMI 38, overall rates of TIMI Major or Minor bleeding adverse reactions unrelated to coronary artery bypass graft surgery (CABG) were significantly higher on Effient than on clopidogrel, as shown in Table 1.

Table 1: Non-CABG-Related Bleeding [Patients may be counted in more than one row.] (TRITON-TIMI 38)
 | Effient (%) (N=6741) | Clopidogrel (%) (N=6716)
TIMI Major or Minor bleeding | 4.5 | 3.4
TIMI Major bleeding [See 5.1 for definition.] | 2.2 | 1.7
Life-threatening | 1.3 | 0.8
Fatal | 0.3 | 0.1
Symptomatic intracranial hemorrhage (ICH) | 0.3 | 0.3
Requiring inotropes | 0.3 | 0.1
Requiring surgical intervention | 0.3 | 0.3
Requiring transfusion (≥4 units) | 0.7 | 0.5
TIMI Minor bleeding | 2.4 | 1.9

Figure 1 demonstrates non-CABG-related TIMI Major or Minor bleeding. The bleeding rate is highest initially, as shown in Figure 1 (inset: Days 0 to 7) [see Warnings and Precautions (5.1)] .

Bleeding by Weight and Age

In TRITON-TIMI 38, non-CABG-related TIMI Major or Minor bleeding rates in patients with the risk factors of age ≥75 years and weight <60 kg are shown in Table 2.

Table 2: Bleeding Rates for Non-CABG-Related Bleeding by Weight and Age (TRITON-TIMI 38)
 | Major/Minor |  | Fatal
 | Effient [10 mg Effient maintenance dose] (%) | Clopidogrel [75 mg clopidogrel maintenance dose] (%) | Effient (%) | Clopidogrel (%)
Weight <60 kg (N=308 Effient, N=356 clopidogrel) | 10.1 | 6.5 | 0.0 | 0.3
Weight ≥60 kg (N=6373 Effient, N=6299 clopidogrel) | 4.2 | 3.3 | 0.3 | 0.1
Age <75 years (N=5850 Effient, N=5822 clopidogrel) | 3.8 | 2.9 | 0.2 | 0.1
Age ≥75 years (N=891 Effient, N=894 clopidogrel) | 9.0 | 6.9 | 1.0 | 0.1

Bleeding Related to CABG

In TRITON-TIMI 38, 437 patients who received a thienopyridine underwent CABG during the course of the study. The rate of CABG-related TIMI Major or Minor bleeding was 14.1% for the Effient group and 4.5% in the clopidogrel group (see Table 3). The higher risk for bleeding adverse reactions in patients treated with Effient persisted up to 7 days from the most recent dose of study drug.

Table 3: CABG-Related Bleeding [Patients may be counted in more than one row.] (TRITON-TIMI 38)
 | Effient (%) (N=213) | Clopidogrel (%) (N=224)
TIMI Major or Minor bleeding | 14.1 | 4.5
TIMI Major bleeding | 11.3 | 3.6
Fatal | 0.9 | 0
Reoperation | 3.8 | 0.5
Transfusion of ≥5 units | 6.6 | 2.2
Intracranial hemorrhage | 0 | 0
TIMI Minor bleeding | 2.8 | 0.9

Bleeding Reported as Adverse Reactions

Hemorrhagic events reported as adverse reactions in TRITON-TIMI 38 were, for Effient and clopidogrel, respectively: epistaxis (6.2%, 3.3%), gastrointestinal hemorrhage (1.5%, 1.0%), hemoptysis (0.6%, 0.5%), subcutaneous hematoma (0.5%, 0.2%), post-procedural hemorrhage (0.5%, 0.2%), retroperitoneal hemorrhage (0.3%, 0.2%), pericardial effusion/hemorrhage/tamponade (0.3%, 0.2%), and retinal hemorrhage (0.0%, 0.1%).

Malignancies

During TRITON-TIMI 38, newly diagnosed malignancies were reported in 1.6% and 1.2% of patients treated with prasugrel and clopidogrel, respectively. The sites contributing to the differences were primarily colon and lung. In another Phase 3 clinical study of ACS patients not undergoing PCI, in which data for malignancies were prospectively collected, newly diagnosed malignancies were reported in 1.8% and 1.7% of patients treated with prasugrel and clopidogrel, respectively. The site of malignancies was balanced between treatment groups except for colorectal malignancies. The rates of colorectal malignancies were 0.3% prasugrel, 0.1% clopidogrel and most were detected during investigation of GI bleed or anemia. It is unclear if these observations are causally related, are the result of increased detection because of bleeding, or are random occurrences.

Other Adverse Events

In TRITON-TIMI 38, common and other important nonhemorrhagic adverse events were, for Effient and clopidogrel, respectively: severe thrombocytopenia (0.06%, 0.04%), anemia (2.2%, 2.0%), abnormal hepatic function (0.22%, 0.27%), allergic reactions (0.36%, 0.36%), and angioedema (0.06%, 0.04%). Table 4 summarizes the adverse events reported by at least 2.5% of patients.

Table 4: Non-Hemorrhagic Treatment Emergent Adverse Events Reported by at Least 2.5% of Patients in Either Group
 | Effient (%) (N=6741) | Clopidogrel (%) (N=6716)
Hypertension | 7.5 | 7.1
Hypercholesterolemia/Hyperlipidemia | 7.0 | 7.4
Headache | 5.5 | 5.3
Back pain | 5.0 | 4.5
Dyspnea | 4.9 | 4.5
Nausea | 4.6 | 4.3
Dizziness | 4.1 | 4.6
Cough | 3.9 | 4.1
Hypotension | 3.9 | 3.8
Fatigue | 3.7 | 4.8
Noncardiac chest pain | 3.1 | 3.5
Atrial fibrillation | 2.9 | 3.1
Bradycardia | 2.9 | 2.4
Leukopenia (<4 × 10^9 WBC [WBC = white blood cell] /L) | 2.8 | 3.5
Rash | 2.8 | 2.4
Pyrexia | 2.7 | 2.2
Peripheral edema | 2.7 | 3.0
Pain in extremity | 2.6 | 2.6
Diarrhea | 2.3 | 2.6

6.2 Postmarketing Experience

The following adverse reactions have been identified during post-approval use of Effient. Because these reactions are reported voluntarily from a population of uncertain size, it is not always possible to reliably estimate their frequency or establish a causal relationship to drug exposure.

Blood and lymphatic system disorders — thrombocytopenia, thrombotic thrombocytopenic purpura (TTP) [see Warnings and Precautions (5.4) and Patient Counseling Information (17)]

Immune system disorders — hypersensitivity reactions including anaphylaxis [see Contraindications (4.3)]

7 DRUG INTERACTIONS

7.1 Warfarin

Coadministration of Effient and warfarin increases the risk of bleeding [see Warnings and Precautions (5.1) and Clinical Pharmacology (12.3)] .

7.2 Nonsteroidal Anti-Inflammatory Drugs

Coadministration of Effient and NSAIDs (used chronically) may increase the risk of bleeding [see Warnings and Precautions (5.1)] .

7.3 Opioids

As with other oral P2Y12 inhibitors, coadministration of opioid agonists delay and reduce the absorption of prasugrel's active metabolite presumably because of slowed gastric emptying [see Clinical Pharmacology (12.3)] . Consider the use of a parenteral anti-platelet agent in acute coronary syndrome patients requiring coadministration of morphine or other opioid agonists.

7.4 Other Concomitant Medications

Effient can be administered with drugs that are inducers or inhibitors of cytochrome P450 enzymes [see Clinical Pharmacology (12.3)] .

Effient can be administered with aspirin (75 mg to 325 mg per day), heparin, GPIIb/IIIa inhibitors, statins, digoxin, and drugs that elevate gastric pH, including proton pump inhibitors and H2 blockers [see Clinical Pharmacology (12.3)] .

8 USE IN SPECIFIC POPULATIONS

8.1 Pregnancy

Risk Summary

There are no data with Effient use in pregnant women to inform a drug-associated risk. No structural malformations were observed in animal reproductive and developmental toxicology studies when rats and rabbits were administered prasugrel during organogenesis at doses of up to 30 times the recommended therapeutic exposures in humans [see Data]. Due to the mechanism of action of Effient, and the associated identified risk of bleeding, consider the benefits and risks of Effient and possible risks to the fetus when prescribing Effient to a pregnant woman [see Boxed Warning and Warnings and Precautions (5.1, 5.3)] .

The background risk of major birth defects and miscarriage for the indicated population is unknown. The background risk in the U.S. general population of major birth defects is 2-4% and of miscarriage is 15-20% of clinically recognized pregnancies.

Data

Animal Data

In embryo-fetal developmental toxicology studies, pregnant rats and rabbits received prasugrel at maternally toxic oral doses equivalent to more than 40 times the human exposure. A slight decrease in fetal body weight was observed, but there were no structural malformations in either species. In prenatal and postnatal rat studies, maternal treatment with prasugrel had no effect on the behavioral or reproductive development of the offspring at doses greater than 150 times the human exposure.

8.2 Lactation

Risk Summary

There is no information regarding the presence of prasugrel in human milk, the effects on the breastfed infant, or the effects on milk production. Metabolites of prasugrel were found in rat milk [see Data] . The developmental and health benefits of breastfeeding should be considered along with the mother's clinical need for Effient and any potential adverse effects on the breastfed child from Effient or from the underlying maternal condition.

Data

Animal Data

Following a 5 mg/kg oral dose of [^14C]-prasugrel to lactating rats, metabolites of prasugrel were detected in the maternal milk and blood.

8.4 Pediatric Use

Safety and effectiveness in pediatric patients have not been established.

In a randomized, placebo-controlled trial, the primary objective of reducing the rate of vaso-occlusive crisis (painful crisis or acute chest syndrome) in pediatric patients, aged 2 to less than 18 years, with sickle cell anemia was not met.

8.5 Geriatric Use

In TRITON-TIMI 38, 38.5% of patients were ≥65 years of age and 13.2% were ≥75 years of age. The risk of bleeding increased with advancing age in both treatment groups, although the relative risk of bleeding (Effient compared with clopidogrel) was similar across age groups.

Patients ≥75 years of age who received Effient 10 mg had an increased risk of fatal bleeding events (1.0%) compared to patients who received clopidogrel (0.1%). In patients ≥75 years of age, symptomatic intracranial hemorrhage occurred in 7 patients (0.8%) who received Effient and in 3 patients (0.3%) who received clopidogrel. Because of the risk of bleeding, and because effectiveness is uncertain in patients ≥75 years of age [see Clinical Studies (14)] , use of Effient is generally not recommended in these patients, except in high-risk situations (diabetes and past history of myocardial infarction) where its effect appears to be greater and its use may be considered [see Warnings and Precautions (5.1), Clinical Pharmacology (12.3), and Clinical Studies (14)] .

8.6 Low Body Weight

In TRITON-TIMI 38, 4.6% of patients treated with Effient had body weight <60 kg. Individuals with body weight <60 kg had an increased risk of bleeding and an increased exposure to the active metabolite of prasugrel [see Dosage and Administration (2), Warnings and Precautions (5.1), and Clinical Pharmacology (12.3)] . Consider lowering the maintenance dose to 5 mg in patients <60 kg. The effectiveness and safety of the 5 mg dose have not been prospectively studied [see Dosage and Administration (2) and Clinical Pharmacology (12.3)] .

8.7 Renal Impairment

No dosage adjustment is necessary for patients with renal impairment. There is limited experience in patients with end-stage renal disease, but such patients are generally at higher risk of bleeding [see Warnings and Precautions (5.1) and Clinical Pharmacology (12.3)] .

8.8 Hepatic Impairment

No dosage adjustment is necessary in patients with mild to moderate hepatic impairment (Child-Pugh Class A and B). The pharmacokinetics and pharmacodynamics of prasugrel in patients with severe hepatic disease have not been studied, but such patients are generally at higher risk of bleeding [see Warnings and Precautions (5.1) and Clinical Pharmacology (12.3)] .

8.9 Metabolic Status

In healthy subjects, patients with stable atherosclerosis, and patients with ACS receiving prasugrel, there was no relevant effect of genetic variation in CYP2B6, CYP2C9, CYP2C19, or CYP3A5 on the pharmacokinetics of prasugrel's active metabolite or its inhibition of platelet aggregation.

10 OVERDOSAGE

10.1 Signs and Symptoms

Platelet inhibition by prasugrel is rapid and irreversible, lasting for the life of the platelet, and is unlikely to be increased in the event of an overdose. In rats, lethality was observed after administration of 2000 mg/kg. Symptoms of acute toxicity in dogs included emesis, increased serum alkaline phosphatase, and hepatocellular atrophy. Symptoms of acute toxicity in rats included mydriasis, irregular respiration, decreased locomotor activity, ptosis, staggering gait, and lacrimation.

10.2 Recommendations about Specific Treatment

Platelet transfusion may restore clotting ability. The prasugrel active metabolite is not likely to be removed by dialysis.

11 DESCRIPTION

Effient contains prasugrel, a thienopyridine class inhibitor of platelet activation and aggregation mediated by the P2Y12 ADP receptor. Effient is formulated as the hydrochloride salt, a racemate, which is chemically designated as 5-[(1RS)-2-cyclopropyl-1-(2-fluorophenyl)-2-oxoethyl]-4,5,6,7-tetrahydrothieno[3,2-c] pyridin-2-yl acetate hydrochloride. Prasugrel hydrochloride has the empirical formula C20H20FNO3S∙HCl representing a molecular weight of 409.90. The chemical structure of prasugrel hydrochloride is:

Prasugrel hydrochloride is a white to practically white solid. It is soluble at pH 2, slightly soluble at pH 3 to 4, and practically insoluble at pH 6 to 7.5. It also dissolves freely in methanol and is slightly soluble in 1- and 2-propanol and acetone. It is practically insoluble in diethyl ether and ethyl acetate.

Effient is available for oral administration as 5 mg or 10 mg elongated hexagonal, film-coated, non-scored tablets, debossed on each side. Each yellow 5 mg tablet is manufactured with 5.49 mg prasugrel hydrochloride, equivalent to 5 mg prasugrel and each beige 10 mg tablet with 10.98 mg prasugrel hydrochloride, equivalent to 10 mg of prasugrel.

Other ingredients include mannitol, hypromellose, low-substituted hydroxypropyl cellulose, microcrystalline cellulose, sucrose stearate, and glyceryl behenate. The color coatings contain lactose, hypromellose, titanium dioxide, triacetin, iron oxide yellow, and iron oxide red (only in Effient 10 mg tablet).

12 CLINICAL PHARMACOLOGY

12.1 Mechanism of Action

Prasugrel is an inhibitor of platelet activation and aggregation through the irreversible binding of its active metabolite to the P2Y12 class of ADP receptors on platelets.

12.2 Pharmacodynamics

Prasugrel produces inhibition of platelet aggregation to 20 µM or 5 µM ADP, as measured by light transmission aggregometry. Following a 60 mg loading dose of Effient, approximately 90% of patients had at least 50% inhibition of platelet aggregation by 1 hour. Maximum platelet inhibition was about 80% (see Figure 2). Mean steady-state inhibition of platelet aggregation was about 70% following 3 to 5 days of dosing at 10 mg daily after a 60 mg loading dose of Effient.

Figure 2: Inhibition (Mean ± SD) of 20 µM ADP-induced Platelet Aggregation (IPA) Measured by Light Transmission Aggregometry after Prasugrel 60 mg

Platelet aggregation gradually returns to baseline values over 5-9 days after discontinuation of prasugrel, this time course being a reflection of new platelet production rather than pharmacokinetics of prasugrel. Discontinuing clopidogrel 75 mg and initiating a prasugrel 10 mg maintenance dose with or without a prasugrel 60 mg loading dose results in a decrease of 14 percentage points in maximum platelet aggregation (MPA) by Day 7. This decrease in MPA is not greater than that typically produced by a 10 mg maintenance dose of prasugrel alone. The relationship between inhibition of platelet aggregation and clinical activity has not been established.

5 mg in Low Body Weight Patients

In patients with stable coronary artery disease, mean platelet inhibition in subjects <60 kg taking 5 mg prasugrel was similar to that of subjects ≥60 kg taking 10 mg prasugrel. The relationship between inhibition of platelet aggregation and clinical activity has not been established.

12.3 Pharmacokinetics

Prasugrel is a prodrug and is rapidly metabolized to a pharmacologically active metabolite and inactive metabolites. The active metabolite has an elimination half-life of about 7 hours (range 2-15 hours). Healthy subjects, patients with stable atherosclerosis, and patients undergoing PCI show similar pharmacokinetics.

Absorption and Binding

Following oral administration, ≥79% of the dose is absorbed. The absorption and metabolism are rapid, with peak plasma concentrations (Cmax) of the active metabolite occurring approximately 30 minutes after dosing. The active metabolite's exposure (AUC) increases slightly more than proportionally over the dose range of 5 to 60 mg. Repeated daily doses of 10 mg do not lead to accumulation of the active metabolite. In a study of healthy subjects given a single 15 mg dose, the AUC of the active metabolite was unaffected by a high-fat, high-calorie meal, but Cmax was decreased by 49% and Tmax was increased from 0.5 to 1.5 hours. Effient can be administered without regard to food. The active metabolite is bound about 98% to human serum albumin.

Metabolism and Elimination

Prasugrel is not detected in plasma following oral administration. It is rapidly hydrolyzed in the intestine to a thiolactone, which is then converted to the active metabolite by a single step, primarily by CYP3A4 and CYP2B6 and to a lesser extent by CYP2C9 and CYP2C19. The estimates of apparent volume of distribution of prasugrel's active metabolite ranged from 44 to 68 L and the estimates of apparent clearance ranged from 112 to 166 L/hr in healthy subjects and patients with stable atherosclerosis. The active metabolite is metabolized to two inactive compounds by S-methylation or conjugation with cysteine. The major inactive metabolites are highly bound to human plasma proteins. Approximately 68% of the prasugrel dose is excreted in the urine and 27% in the feces as inactive metabolites.

Specific Populations

Geriatric Patients

In a study of 32 healthy subjects between the ages of 20 and 80 years, age had no significant effect on pharmacokinetics of prasugrel's active metabolite or its inhibition of platelet aggregation. In TRITON-TIMI 38, the mean exposure (AUC) of the active metabolite was 19% higher in patients ≥75 years of age than in patients <75 years of age. In a study in subjects with stable atherosclerosis, the mean exposure (AUC) to the active metabolite of prasugrel in subjects ≥75 years old taking a 5 mg maintenance dose was approximately half that seen in subjects 45 to 64 years old taking a 10 mg maintenance dose [see Warnings and Precautions (5.1) and Use in Specific Populations (8.5)] .

Body Weight

The mean exposure (AUC) to the active metabolite is approximately 30 to 40% higher in subjects with a body weight of <60 kg than in those weighing ≥60 kg. In a study in subjects with stable atherosclerosis, the AUC of the active metabolite on average was 38% lower in subjects <60 kg taking 5 mg (N=34) than in subjects ≥60 kg taking 10 mg (N=38) [see Dosage and Administration (2), Warnings and Precautions (5.1), Adverse Reactions (6.1), and Use in Specific Populations (8.6)] .

Male and Female Patients

Pharmacokinetics of prasugrel's active metabolite is similar in men and women.

Racial or Ethnic Groups

Exposure in subjects of African and Hispanic descent is similar to that in Caucasians. In clinical pharmacology studies, after adjusting for body weight, the AUC of the active metabolite was approximately 19% higher in Chinese, Japanese, and Korean subjects than in Caucasian subjects.

Smoking

Pharmacokinetics of prasugrel's active metabolite is similar in smokers and nonsmokers.

Patients with Renal Impairment

Pharmacokinetics of prasugrel's active metabolite and its inhibition of platelet aggregation is similar in patients with moderate renal impairment (CrCL=30 to 50 mL/min) and healthy subjects. In patients with end-stage renal disease, exposure to the active metabolite (both Cmax and AUC (0-tlast)) was about half that in healthy controls and patients with moderate renal impairment [see Warnings and Precautions (5.1) and Use in Specific Populations (8.7)] .

Patients with Hepatic Impairment

Pharmacokinetics of prasugrel's active metabolite and inhibition of platelet aggregation was similar in patients with mild to moderate hepatic impairment compared to healthy subjects. The pharmacokinetics and pharmacodynamics of prasugrel's active metabolite in patients with severe hepatic disease have not been studied [see Warnings and Precautions (5.1) and Use in Specific Populations (8.8)] .

Drug Interaction Studies

Potential for Other Drugs to Affect Prasugrel

Inhibitors of CYP3A - Ketoconazole (400 mg daily), a selective and potent inhibitor of CYP3A4 and CYP3A5, did not affect prasugrel-mediated inhibition of platelet aggregation or the active metabolite's AUC and Tmax, but decreased the Cmax by 34% to 46%. Therefore, CYP3A inhibitors such as verapamil, diltiazem, indinavir, ciprofloxacin, clarithromycin, and grapefruit juice are not expected to have a significant effect on the pharmacokinetics of the active metabolite of prasugrel [see Drug Interactions (7.4)] .

Inducers of Cytochromes P450 - Rifampicin (600 mg daily), a potent inducer of CYP3A and CYP2B6 and an inducer of CYP2C9, CYP2C19, and CYP2C8, did not significantly change the pharmacokinetics of prasugrel's active metabolite or its inhibition of platelet aggregation. Therefore, known CYP3A inducers such as rifampicin, carbamazepine, and other inducers of cytochromes P450 are not expected to have significant effect on the pharmacokinetics of the active metabolite of prasugrel [see Drug Interactions (7.4)] .

Drugs that Elevate Gastric pH - Daily coadministration of ranitidine (an H2 blocker) or lansoprazole (a proton pump inhibitor) decreased the Cmax of the prasugrel active metabolite by 14% and 29%, respectively, but did not change the active metabolite's AUC and Tmax. In TRITON-TIMI 38, Effient was administered without regard to coadministration of a proton pump inhibitor or H2 blocker [see Drug Interactions (7.4)] .

Statins - Atorvastatin (80 mg daily), a drug metabolized by CYP450 3A4, did not alter the pharmacokinetics of prasugrel's active metabolite or its inhibition of platelet aggregation [see Drug Interactions (7.4)] .

Heparin - A single intravenous dose of unfractionated heparin (100 units/kg) did not significantly alter coagulation or the prasugrel-mediated inhibition of platelet aggregation; however, bleeding time was increased compared with either drug alone [see Drug Interactions (7.4)] .

Aspirin - Aspirin 150 mg daily did not alter prasugrel-mediated inhibition of platelet aggregation; however, bleeding time was increased compared with either drug alone [see Drug Interactions (7.4)] .

Warfarin - A significant prolongation of the bleeding time was observed when prasugrel was coadministered with 15 mg of warfarin [see Drug Interactions (7.1)] .

Potential for Prasugrel to Affect Other Drugs

In vitro metabolism studies demonstrate that prasugrel's main circulating metabolites are not likely to cause clinically significant inhibition of CYP1A2, CYP2C9, CYP2C19, CYP2D6, or CYP3A, or induction of CYP1A2 or CYP3A.

Drugs Metabolized by CYP2B6 - Prasugrel is a weak inhibitor of CYP2B6. In healthy subjects, prasugrel decreased exposure to hydroxybupropion, a CYP2B6-mediated metabolite of bupropion, by 23%, an amount not considered clinically significant. Prasugrel is not anticipated to have significant effect on the pharmacokinetics of drugs that are primarily metabolized by CYP2B6, such as halothane, cyclophosphamide, propofol, and nevirapine.

Effect on Digoxin - The potential role of prasugrel as a Pgp substrate was not evaluated. Prasugrel is not an inhibitor of Pgp, as digoxin clearance was not affected by prasugrel coadministration [see Drug Interactions (7.4)] .

Morphine - Coadministration of 5 mg intravenous morphine with 60 mg loading dose of prasugrel in healthy adults decreased the Cmax of prasugrel's active metabolite by 31% with no change in AUC, Tmax, or inhibition of ADP-induced platelet aggregation. ADP-induced platelet aggregation was higher up to 2 hours following 60 mg loading dose of prasugrel in stable patients more than 1 year after an ACS who were coadministered morphine. In the patients with a 2-hour delay in the onset of platelet aggregation (5 of 11), Tmax was delayed and prasugrel active metabolite levels were significantly lower at 30 min (5 vs 120 ng/mL) following coadministration with morphine.

12.5 Pharmacogenomics

There is no relevant effect of genetic variation in CYP2B6, CYP2C9, CYP2C19, or CYP3A5 on the pharmacokinetics of prasugrel's active metabolite or its inhibition of platelet aggregation.

13 NONCLINICAL TOXICOLOGY

13.1 Carcinogenesis, Mutagenesis, Impairment of Fertility

Carcinogenesis

No compound-related tumors were observed in a 2-year rat study with prasugrel at oral doses up to 100 mg/kg/day (>100 times the recommended therapeutic exposures in humans [based on plasma exposures to the major circulating human metabolite]). There was an increased incidence of tumors (hepatocellular adenomas) in mice exposed for 2 years to high doses (>250 times the human metabolite exposure).

Mutagenesis

Prasugrel was not genotoxic in two in vitro tests (Ames bacterial gene mutation test, clastogenicity assay in Chinese hamster fibroblasts) and in one in vivo test (micronucleus test by intraperitoneal route in mice).

Impairment of Fertility

Prasugrel had no effect on fertility of male and female rats at oral doses up to 300 mg/kg/day (80 times the human major metabolite exposure at daily dose of 10 mg prasugrel).

14 CLINICAL STUDIES

The clinical evidence for the effectiveness of Effient is derived from the TRITON-TIMI 38 (TRial to Assess Improvement in Therapeutic Outcomes by Optimizing Platelet Inhibitio N with Prasugrel) study, a 13,608 patient, multicenter, international, randomized, double-blind, parallel-group study comparing Effient to a regimen of clopidogrel, each added to aspirin and other standard therapy, in patients with ACS (UA, NSTEMI, or STEMI) who were to be managed with PCI. Randomization was stratified for UA/NSTEMI and STEMI.

Patients with UA/NSTEMI presenting within 72 hours of symptom onset were to be randomized after undergoing coronary angiography. Patients with STEMI presenting within 12 hours of symptom onset could be randomized prior to coronary angiography. Patients with STEMI presenting between 12 hours and 14 days of symptom onset were to be randomized after undergoing coronary angiography. Patients underwent PCI, and for both UA/NSTEMI and STEMI patients, the loading dose was to be administered anytime between randomization and 1 hour after the patient left the catheterization lab. If patients with STEMI were treated with thrombolytic therapy, randomization could not occur until at least 24 hours (for tenecteplase, reteplase, or alteplase) or 48 hours (for streptokinase) after the thrombolytic was given.

Patients were randomized to receive Effient (60 mg loading dose followed by 10 mg once daily) or clopidogrel (300 mg loading dose followed by 75 mg once daily), with administration and follow-up for a minimum of 6 months (actual median 14.5 months). Patients also received aspirin (75 mg to 325 mg once daily). Other therapies, such as heparin and intravenous glycoprotein IIb/IIIa (GPIIb/IIIa) inhibitors, were administered at the discretion of the treating physician. Oral anticoagulants, other platelet inhibitors, and chronic NSAIDs were not allowed.

The primary outcome measure was the composite of cardiovascular death, nonfatal MI, or nonfatal stroke in the UA/NSTEMI population. Success in this group allowed analysis of the same endpoint in the overall ACS and STEMI populations. Nonfatal MIs included both MIs detected solely through analysis of creatine kinase muscle-brain (CK-MB) changes and clinically apparent (investigator-reported) MIs.

The patient population was 92% Caucasian, 26% female, and 39% ≥65 years of age. The median time from symptom onset to study drug administration was 7 hours for patients with STEMI and 30 hours for patients with UA/NSTEMI. Approximately 99% of patients underwent PCI. The study drug was administered after the first coronary guidewire was placed in approximately 75% of patients.

Effient significantly reduced total endpoint events compared to clopidogrel (see Figure 3 and Table 5). The reduction of total endpoint events was driven primarily by a decrease in nonfatal MIs, both those occurring early (through 3 days) and later (after 3 days). Approximately 40% of MIs occurred peri-procedurally and were detected solely by changes in CK-MB. Administration of the clopidogrel loading dose in TRITON-TIMI 38 was delayed relative to the placebo-controlled trials that supported its approval for ACS. Effient produced higher rates of clinically significant bleeding than clopidogrel in TRITON-TIMI 38 [see Adverse Reactions (6.1)] . Choice of therapy requires balancing these differences in outcome.

The treatment effect of Effient was apparent within the first few days, and persisted to the end of the study (see Figure 3). The inset shows results over the first 7 days.

Figure 3: Time to First Event of CV Death, MI, or Stroke (TRITON-TIMI 38)

The Kaplan-Meier curves (see Figure 3) show the primary composite endpoint of CV death, nonfatal MI, or nonfatal stroke over time in the UA/NSTEMI and STEMI populations. In both populations, the curves separate within the first few hours. In the UA/NSTEMI population, the curves continue to diverge throughout the 15-month follow-up period. In the STEMI population, the early separation was maintained throughout the 15-month follow-up period, but there was no progressive divergence after the first few weeks.

Effient reduced the occurrence of the primary composite endpoint compared to clopidogrel in both the UA/NSTEMI and STEMI populations (see Table 5). In patients who survived an on-study myocardial infarction, the incidence of subsequent events was also lower in the Effient group.

Table 5: Patients with Outcome Events (CV Death, MI, Stroke) in TRITON-TIMI 38
 | Patients with events |  | From Kaplan-Meier analysis
 | Effient (%) | Clopidogrel (%) | Relative Risk Reduction (%) [RRR = (1-Hazard Ratio) × 100%. Values with a negative relative risk reduction indicate a relative risk increase.] (95% CI) | p-value
UA/NSTEMI | N=5044 | N=5030
CV death, nonfatal MI, or nonfatal stroke | 9.3 | 11.2 | 18.0 (7.3, 27.4) | 0.002
CV death | 1.8 | 1.8 | 2.1 (-30.9, 26.8) | 0.885
Nonfatal MI | 7.1 | 9.2 | 23.9 (12.7, 33.7) | <0.001
Nonfatal Stroke | 0.8 | 0.8 | 2.1 (-51.3, 36.7) | 0.922
STEMI | N=1769 | N=1765
CV death, nonfatal MI, or nonfatal stroke | 9.8 | 12.2 | 20.7 (3.2, 35.1) | 0.019
CV death | 2.4 | 3.3 | 26.2 (-9.4, 50.3) | 0.129
Nonfatal MI | 6.7 | 8.8 | 25.4 (5.2, 41.2) | 0.016
Nonfatal Stroke | 1.2 | 1.1 | -9.7 (-104.0, 41.0) | 0.77

The effect of Effient in various subgroups is shown in Figures 4 and 5. Results are generally consistent across pre-specified subgroups, with the exception of patients with a history of TIA or stroke [see Contraindications (4.2)] . The treatment effect was driven primarily by a reduction in nonfatal MI. The effect in patients ≥75 years of age was also somewhat smaller, and bleeding risk is higher in these individuals [see Adverse Reactions (6.1)] . See below for analyses of patients ≥75 years of age with risk factors.

Figure 4: Subgroup Analyses for Time to First Event of CV Death, MI, or Stroke (HR and 95% CI; TRITON-TIMI 38) – UA/NSTEMI Patients

Figure 5: Subgroup Analyses for Time to First Event of CV Death, MI, or Stroke (HR and 95% CI; TRITON-TIMI 38) – STEMI Patients

Effient is generally not recommended in patients ≥75 years of age, except in high-risk situations (diabetes mellitus or prior MI) where its effect appears to be greater and its use may be considered. These recommendations are based on subgroup analyses (see Table 6) and must be interpreted with caution, but the data suggest that Effient reduces ischemic events in such patients.

Table 6: Subgroup Analyses for Time to First Event of CV Death, MI, or Stroke: Patients < or ≥75 Years of Age, ± Diabetes, ± Prior History of MI, All ACS Patient Population
 | Effient |  | Clopidogrel |  | Hazard Ratio (95% CI)
 | N | % with events | N | % with events | Hazard Ratio (95% CI)
Age ≥75
Diabetes – yes | 249 | 14.9 | 234 | 21.8 | 0.64 (0.42, 0.97)
Diabetes – no | 652 | 16.4 | 674 | 15.3 | 1.1 (0.83, 1.43)
Age <75
Diabetes – yes | 1327 | 10.8 | 1336 | 14.8 | 0.72 (0.58, 0.89)
Diabetes – no | 4585 | 7.8 | 4551 | 9.5 | 0.82 (0.71, 0.94)
Age ≥75
Prior MI – yes | 220 | 17.3 | 212 | 22.6 | 0.72 (0.47, 1.09)
Prior MI – no | 681 | 15.6 | 696 | 15.2 | 1.05 (0.80, 1.37)
Age <75
Prior MI – yes | 1006 | 12.2 | 996 | 15.4 | 0.78 (0.62, 0.99)
Prior MI – no | 4906 | 7.7 | 4891 | 9.7 | 0.78 (0.68, 0.90)

There were 50% fewer stent thromboses (95% C.I. 32% - 64%; p<0.001) reported among patients randomized to Effient (0.9%) than among patients randomized to clopidogrel (1.8%). The difference manifested early and was maintained through one year of follow-up. Findings were similar with bare metal and drug-eluting stents.

In TRITON-TIMI 38, prasugrel reduced ischemic events (mainly nonfatal MIs) and increased bleeding events [see Adverse Reactions (6.1)] relative to clopidogrel. The findings are consistent with the intended greater inhibition of platelet aggregation by prasugrel at the doses used in the study [see Clinical Pharmacology (12.2)] . There is, however, an alternative explanation: both prasugrel and clopidogrel are prodrugs that must be metabolized to their active moieties. Whereas the pharmacokinetics of prasugrel's active metabolite is not known to be affected by genetic variations in CYP2B6, CYP2C9, CYP2C19, or CYP3A5, the pharmacokinetics of clopidogrel's active metabolite is affected by CYP2C19 genotype, and approximately 30% of Caucasians are reduced metabolizers. Moreover, certain proton pump inhibitors, widely used in the ACS patient population and used in TRITON-TIMI 38, inhibit CYP2C19, thereby decreasing formation of clopidogrel's active metabolite. Thus, reduced-metabolizer status and use of proton pump inhibitors may diminish clopidogrel's activity in a fraction of the population, and may have contributed to prasugrel's greater treatment effect and greater bleeding rate in TRITON-TIMI 38. The extent to which these factors were operational, however, is unknown.

16 HOW SUPPLIED/STORAGE AND HANDLING

16.1 How Supplied

Effient (prasugrel) is available as elongated hexagonal, film-coated, non-scored tablets in the following strengths, colors, debossing, and presentations:

Features | Strengths
Features | 5 mg | 10 mg
Tablet color | yellow | beige
Tablet debossing | 5 | 10
Tablet debossing | 5121 | 5123
Presentations and NDC Codes
Bottles of 30 | 0713-0881-30 | 0713-0882-30

16.2 Storage and Handling

Store at 25°C (77°F); excursions permitted to 15° to 30°C (59° to 86°F) [see USP controlled room temperature].

Keep and dispense only in original container. Keep container closed and do not remove desiccant from bottle. Do not break the tablet.

17 PATIENT COUNSELING INFORMATION

Advise the patient to read the FDA-approved patient labeling (Medication Guide).

Administration

- Advise patients not to break Effient tablets.
- Remind patients not to discontinue Effient without first discussing it with the physician who prescribed Effient [see Warnings and Precautions (5.3)] .
- Inform patients to keep Effient in the container in which it comes, and keep the container closed tightly with the gray cylinder (desiccant) inside.

Bleeding

Inform patients that they:

- will bruise and bleed more easily.
- will take longer than usual to stop bleeding.
- should report any unanticipated, prolonged, or excessive bleeding, or blood in their stool or urine [see Warnings and Precautions (5.1)] .

Thrombotic Thrombocytopenic Purpura

- Inform patients that TTP is a rare but serious condition that has been reported with Effient.
- Instruct patients to get prompt medical attention if they experience symptoms of TTP that cannot otherwise be explained [see Warnings and Precautions (5.4)] .

Hypersensitivity

Inform patients that they may have hypersensitivity reactions and to seek immediate medical attention if any signs and symptoms of a hypersensitivity reaction occur. Patients who have had hypersensitivity reactions to other thienopyridines may have hypersensitivity reactions to Effient.

Invasive Procedures

Instruct patients to:

- inform physicians and dentists that they are taking Effient before any invasive procedure is scheduled [see Warnings and Precautions (5.1)] .
- tell the doctor performing the invasive procedure to talk to the prescribing healthcare professional before stopping Effient.

Concomitant Medications

Ask patients to list all prescription medications, over-the-counter medications, or dietary supplements they are taking or plan to take so the physician knows about other treatments that may affect bleeding risk (e.g., warfarin and NSAIDs) [see Drug Interactions (7.1, 7.2)].

Marketed by Cosette Pharmaceuticals, Inc., South Plainfield, NJ 07080
Effient® is a registered trademark of Cosette Pharmaceuticals, Inc.

8-EFFCP1 Revised: 02/2022

Medication Guide
EFFIENT® (Ef´-fee-ent)
(prasugrel) tablets

What is the most important information I should know about Effient?
Effient is used to lower your chance of having a heart attack or other serious problems with your heart or blood vessels. But, Effient can cause bleeding, which can be serious, and sometimes lead to death. You should not start to take Effient if it is likely that you will have heart bypass surgery (coronary artery bypass graft surgery or CABG) right away. You have a higher risk of bleeding if you take Effient and then have heart bypass surgery.

What is Effient?
Effient is a prescription medicine used to treat people who:

- have had a heart attack or severe chest pain that happens when your heart does not get enough oxygen, and
- have been treated with a procedure called "angioplasty" (also called balloon angioplasty).

Effient is used to lower your chance of having another serious problem with your heart or blood vessels, such as another heart attack, a stroke, blood clots in your stent, or death.
Platelets are blood cells that help with normal blood clotting. Effient helps prevent platelets from sticking together and forming a clot that can block an artery or a stent.
It is not known if Effient is safe and works in children.

Who should not take Effient?

- Do not take Effient if you:
  - currently have abnormal bleeding, such as stomach or intestinal bleeding, or bleeding in your head
  - have had a stroke or "mini-stroke" (also known as transient ischemic attack or TIA)
  - are allergic to prasugrel or any of the ingredients in Effient. See the end of this Medication Guide for a list of ingredients in Effient.
- Get medical help right away if you think you may be having a stroke or TIA. Symptoms that you may be having a stroke or TIA include:
  - sudden slurring of speech,
  - sudden weakness or numbness in one part of your body,
  - sudden blurry vision, or sudden severe headache.
- If you have a stroke or TIA while taking Effient, your doctor will probably stop your Effient. Follow your doctor's instructions about stopping Effient. Do not stop taking Effient unless your doctor tells you to.
- Before having any surgery, you should talk to your doctor about stopping Effient. If possible, Effient should be stopped at least 1 week (7 days) before any surgery, as instructed by the doctor who prescribed Effient for you.

Your risk of bleeding while taking Effient may be higher if you also:

- have had trauma, such as an accident or surgery
- have stomach or intestine bleeding that is recent or keeps coming back, or you have a stomach ulcer
- have severe liver problems
- have moderate to severe kidney problems
- weigh less than 132 pounds
- take other medicines that increase your risk of bleeding, including:
  - warfarin sodium (Coumadin [The brands listed are trademarks of their respective owners and are not trademarks of Cosette Pharmaceuticals, Inc.] , Jantoven)
  - a medicine that contains heparin
  - other medicines to prevent or treat blood clots
  - regular daily use of nonsteroidal anti-inflammatory drugs (NSAIDs)

Tell your doctor if you take any of these medicines. Ask your doctor if you are not sure if your medicine is one listed above.

- Effient increases your risk of bleeding because it lessens the ability of your blood to clot. While you take Effient:
  - you will bruise and bleed more easily
  - you are more likely to have nose bleeds
  - it will take longer for any bleeding to stop
- Call your doctor right away if you have any of these signs or symptoms of bleeding:
  - unexpected bleeding or bleeding that lasts a long time
  - bleeding that is severe or you cannot control
  - pink or brown urine
  - red or black stool (looks like tar)
  - bruises that happen without a known cause or get larger
  - cough up blood or blood clots
  - vomit blood or your vomit looks like "coffee grounds"
- Do not stop taking Effient without talking to the doctor who prescribes it for you. People who are treated with angioplasty and have a stent, and stop taking Effient too soon, have a higher risk of a blood clot in the stent, having a heart attack, or dying. If you must stop Effient because of bleeding, your risk of a heart attack may be higher. See " What are the possible side effects of Effient?" for more information about side effects.

What should I tell my doctor before taking Effient?
Before you take Effient, tell your doctor about all of your medical conditions, including if you:

- have any bleeding problems.
- have had a stroke or "mini-stroke" (also known as transient ischemic attack or TIA).
- are allergic to any medicines, including clopidogrel (Plavix) or ticlopidine hydrochloride.
- have a history of stomach ulcers, colon polyps, diverticulosis.
- have liver problems.
- have kidney problems.
- have had any recent severe injury or surgery.
- plan to have surgery or a dental procedure. See " What is the most important information I should know about Effient?"
- are pregnant, or are planning to get pregnant. It is not known if Effient will harm your baby.
- are breastfeeding. It is not known if Effient passes into your breast milk. You and your doctor should decide if you will take Effient or breastfeed. You should not do both without talking with your doctor.

Tell all of your doctors and dentists that you are taking Effient. They should talk to the doctor who prescribed Effient for you, before you have any surgery or invasive procedure.
Tell your doctor about all the medicines you take, including prescription and nonprescription medicines, vitamins, and herbal supplements. Certain medicines may increase your risk of bleeding. See " What is the most important information I should know about Effient?"
Know the medicines you take. Keep a list of them and show it to your doctor and pharmacist when you get a new medicine.

How should I take Effient?

- Take Effient exactly as prescribed by your doctor.
- Take Effient one time each day.
- You can take Effient with or without food.
- Do not split Effient tablets.
- Take Effient with aspirin as instructed by your doctor.
- Your doctor will decide how long you should take Effient. Do not stop taking Effient without first talking to the doctor who prescribed it for you. See " What is the most important information I should know about Effient?"
- If you miss a dose, take Effient as soon as you remember. If it is almost time for your next dose, skip the missed dose. Just take the next dose at your regular time. Do not take two doses at the same time unless your doctor tells you to.
- If you take too much Effient, call your local emergency room or poison control center right away.
- Call your doctor or healthcare provider right away if you fall or injure yourself, especially if you hit your head. Your doctor or healthcare provider may need to check you.

What are the possible side effects of Effient?
Effient can cause serious side effects, including:

- See " What is the most important information I should know about Effient?"
- A blood clotting problem called thrombotic thrombocytopenic purpura (TTP).TTP can happen with Effient, sometimes after a short time (less than 2 weeks). TTP is a blood clotting problem where blood clots form in blood vessels and can happen all over the body. TTP needs to be treated in a hospital right away, because you may die. Get medical help right away if you have any of these symptoms and they cannot be explained by another medical condition:
  - purplish spots called purpura on the skin or mucous membranes (such as on the mouth) due to bleeding under the skin
  - paleness or jaundice (a yellowish color of the skin or eyes)
  - feeling tired or weak
  - fever
  - fast heart rate or feeling short of breath
  - headache, speech changes, confusion, coma, stroke, or seizure
  - low amount of urine or urine that is pink-tinged or has blood in it
  - stomach area (abdominal) pain, nausea, vomiting, or diarrhea
  - visual changes
- Serious allergic reactions. Serious allergic reactions can happen with Effient, or if you have had a serious allergic reaction to medicines called thienopyridines, for example clopidogrel (Plavix) or ticlopidine hydrochloride. Get medical help right away if you get any of these symptoms of a severe allergic reaction while taking Effient.
  - swelling or hives of your face, lips, in or around your mouth, or throat
  - trouble breathing or swallowing
  - chest pain or pressure
  - dizziness or fainting

Tell your doctor if you have any side effect that bothers you or that does not go away.
These are not all of the possible side effects of Effient. For more information, ask your doctor or pharmacist.
Call your doctor for medical advice about side effects. You may report side effects to FDA at 1-800-FDA-1088.

How should I store Effient?

- Keep Effient at room temperature between 59°F to 86°F (15°C to 30°C).
- Keep and dispense only in original container.
- Keep the container closed tightly with the gray cylinder inside.
- Protect Effient from moisture.

Keep Effient and all medicines out of the reach of children.

General information about the safe and effective use of Effient
Medicines are sometimes prescribed for purposes other than those listed in a Medication Guide. Do not use Effient for a condition for which it was not prescribed. Do not give your Effient to other people, even if they have the same symptoms you have. It may harm them.
This Medication Guide summarizes the most important information about Effient. If you would like more information about Effient, talk with your doctor or pharmacist.

What are the ingredients in Effient?
Active ingredient: prasugrel
Inactive ingredients: mannitol, hypromellose, low-substituted hydroxypropyl cellulose, microcrystalline cellulose, sucrose stearate, and glyceryl behenate. The color coatings contain lactose, hypromellose, titanium dioxide, triacetin, iron oxide yellow, and iron oxide red (only in Effient 10 mg tablet).
Marketed by Cosette Pharmaceuticals, Inc., South Plainfield, NJ 07080
Effient® is a registered trademark of Cosette Pharmaceuticals, Inc.
For more information, call 1-800-922-1038 or go to www.effient.com.

This Medication Guide has been approved by the U.S. Food and Drug Administration.

8-EFFCP1 Revised: 02/2022

PRINCIPAL DISPLAY PANEL - 5 mg Tablet Bottle Label

30 Tablets
NDC 0713-0881-30

Effient®
(prasugrel) tablets

Rx only

5 mg

Keep and dispense only in original
container. Keep container closed and
do not remove desiccant from bottle.

Dispense accompanying
Medication Guide to each patient.

Cosette Pharmaceuticals, Inc.

PRINCIPAL DISPLAY PANEL - 10 mg Tablet Bottle Label

30 Tablets
NDC 0713-0882-30

Effient®
(prasugrel) tablets

Rx only

10 mg

Keep and dispense only in original
container. Keep container closed and
do not remove desiccant from bottle.

Dispense accompanying
Medication Guide to each patient.

Cosette Pharmaceuticals, Inc.